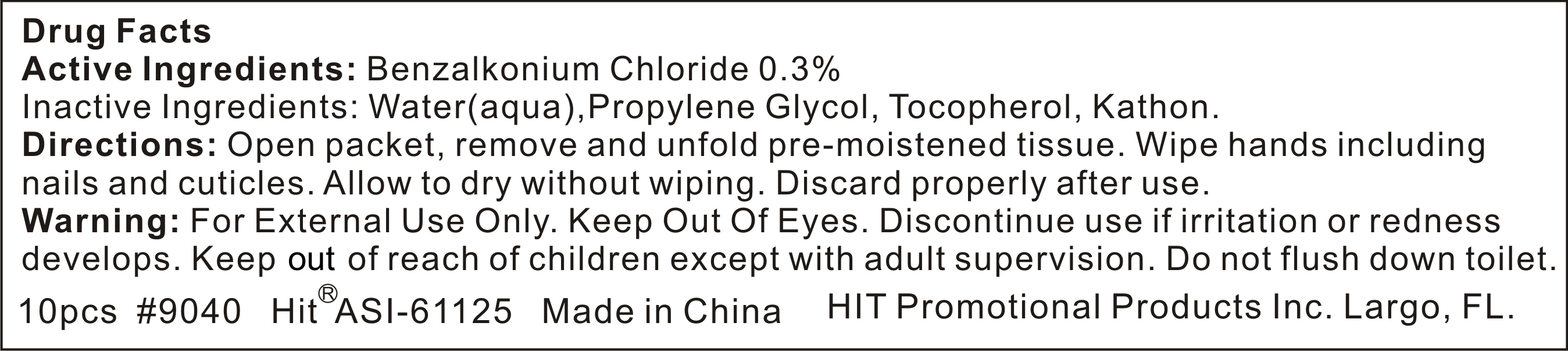 DRUG LABEL: antibacterial wet wipes
NDC: 47993-400 | Form: SWAB
Manufacturer: NINGBO JIANGBEI OCEAN STAR TRADING CO.,LTD
Category: otc | Type: HUMAN OTC DRUG LABEL
Date: 20171206

ACTIVE INGREDIENTS: BENZALKONIUM CHLORIDE 0.3 g/100 g
INACTIVE INGREDIENTS: WATER 95.5 g/100 g; PROPYLENE GLYCOL 4 g/100 g; TOCOPHEROL 0.1 g/100 g; ISOTHIAZOLINONE 0.1 g/100 g

Active Ingredients

Active ingredients:

Benzalkonium Chloride 0.3%

Uses:
Reduces bacteria on the skin. Recommended for repeated use.

Warnings:

For external use only.Keep out of eyes.Discontinue use if irritation or redness develops.Keep out of reach of children except with adult

supervision.Do not flush down toilet.

Directions:

Open packet,remove and unfold pre-moistened tissue.Wipe hands including nails and cuticles.Allow to dry without wiping.Discard properly

after use

Other Information

Do not store above 110F(43C) May discolor certain fabric or surfaces. Harmful to wood finishes and plastics.

KEEP OUT OF REACH OF CHILDREN

Children under 6 years of age should be super vised when using this product.

Inactive Ingredients:

water(aqua),Propylene Glycol,Tocopherol,Kathon